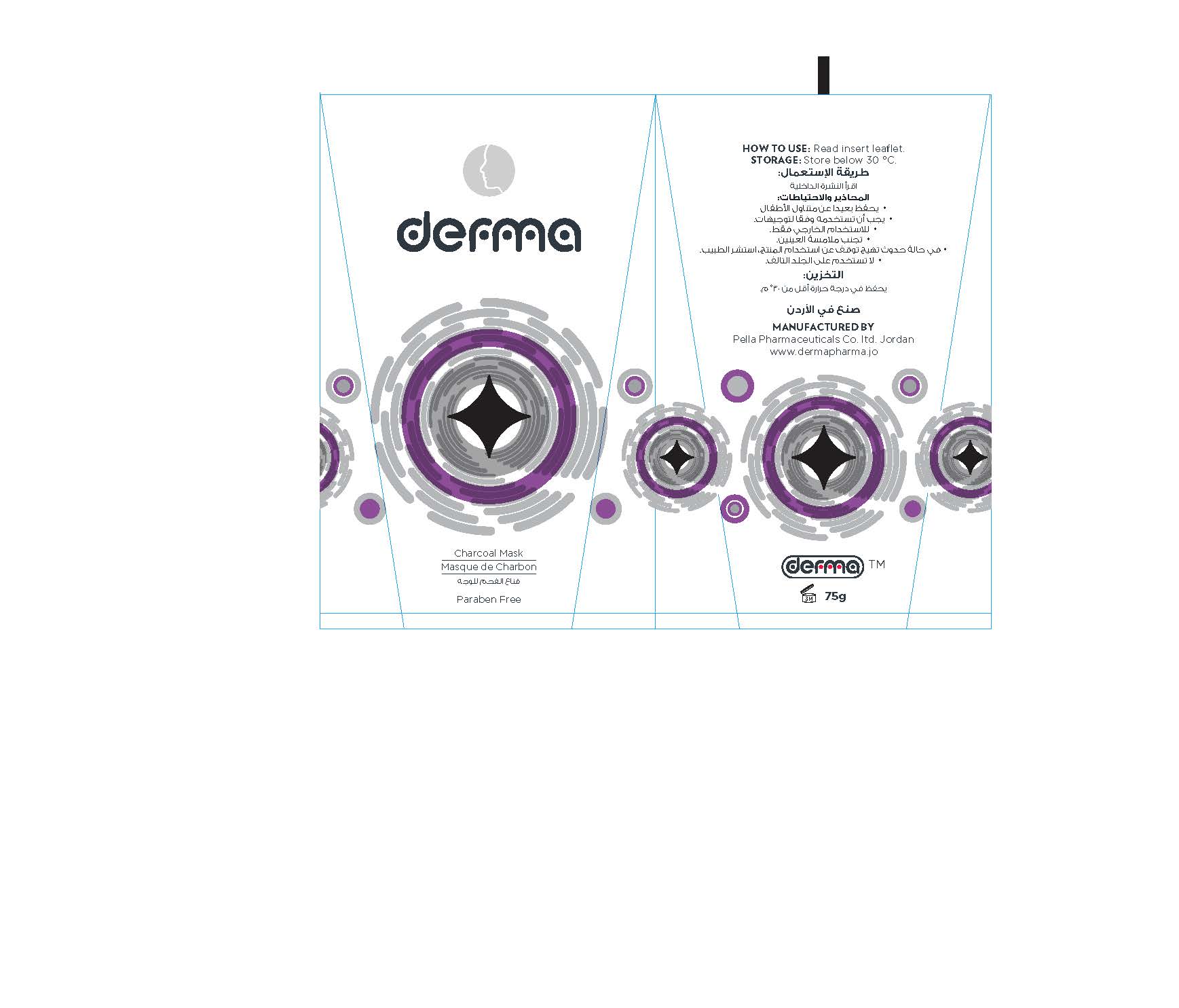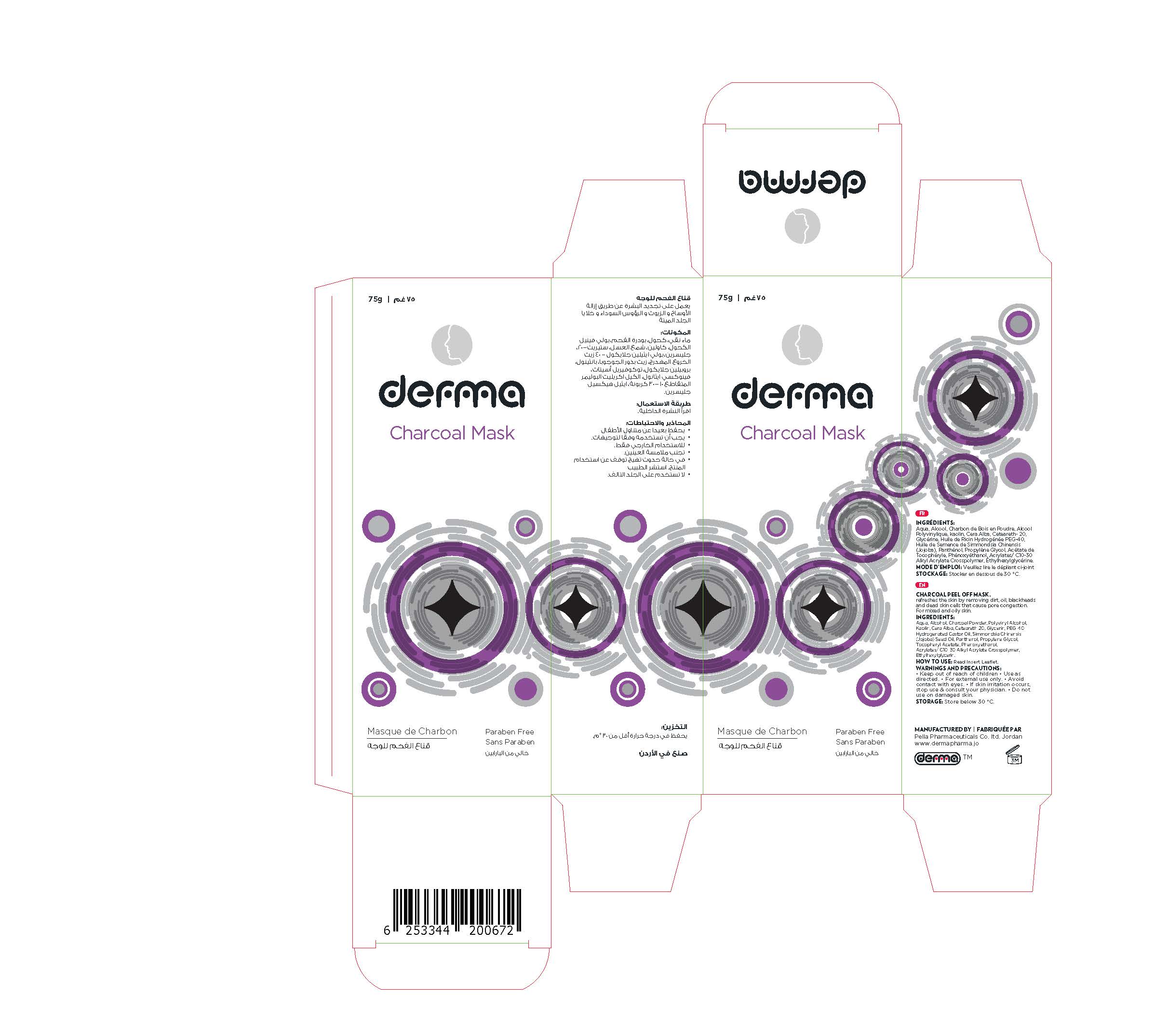 DRUG LABEL: Derma Charcoal Mask
NDC: 82160-672 | Form: GEL
Manufacturer: Pella Pharmaceuticals Co .Ltd
Category: otc | Type: HUMAN OTC DRUG LABEL
Date: 20211121

ACTIVE INGREDIENTS: ACTIVATED CHARCOAL 75 mg/75 g; JOJOBA OIL 15 mg/75 g; DEXPANTHENOL 15 mg/75 g
INACTIVE INGREDIENTS: .ALPHA.-TOCOPHEROL ACETATE, DL-; WATER; POLYVINYL ALCOHOL, UNSPECIFIED; POLYOXYL 40 HYDROGENATED CASTOR OIL; ALCOHOL; KAOLIN; POLYOXYL 20 CETOSTEARYL ETHER; PROPYLENE GLYCOL; CARBOMER INTERPOLYMER TYPE A (ALLYL SUCROSE CROSSLINKED); ETHYLHEXYLGLYCERIN; WHITE WAX; PHENOXYETHANOL; GLYCERIN

Charcoal

Forms and Presentation

Facial Mask: Tube 75 g

Active Ingredients

Charcoal Powder, Simmondsia Chinensis (Jojoba) Seed Oil, Panthenol

Inactive ingredients

Aqua, Alcohol, Polyvinyl Alcohol, Kaolin, Cera Alba (beeswax), Ceteareth-20, Glycerin, PEG-40 Hydrogenated Castor Oil, Propylene Glycol, Tocopheryl Acetate, Phenoxyethanol, Acrylates/ C10-30 Alkyl Acrylate Crosspolymer, Ethylhexylglycerin.

Properties

Charcoal face Mask is an advanced and powerful formula firms and refreshes the skin by removing dirt, oil, blackheads and dead skin cells that cause pore congestion. Draws toxins, chemicals, and other micro-particles to the surface of the skin.
Charcoal Face Mask is recommended for acne-prone, combination, normal and oily skin.

Perfume Free, Paraben Free

Purpose

Facial Mask

Indication

- Detoxifies the skin.
- Remove dull cells, blackheads and dirt.
- Tighten enlarged pores.
- Control facial skin oil, makes your skin beautiful with its power.

Contraindication

Hypersensitivity to any of the components

Precautions

- Must only be used as directed.
- Discontinue use if irritation (redness, pain, etc.) occurs. If skin irritation occurs, consult your physician if the symptoms persist for more than 48 hr.
- Do not use on damaged skin.

Precaution

- Keep out of reach of children

Warnings

- For external use only.
- Avoid contact with eyes.

Pregnancy

Ask your doctor or pharmacist for advice before using any product.
If you want to apply the mask during pregnancy then discuss this with your doctor.

Lactation

Ask your doctor or pharmacist for advice before using any product.
If you want to apply the mask during lactation then discuss this with your doctor.

Interactions

No interactions between this mask and other drugs or substances are known or suspected

Side effects

Irritation (redness, pain, etc.) can be occurring

Dosage and administration

1. Clean the face; open your pores using a warm, moist towel on face for 3- 5 minutes.
2. Gently apply mask on the face using the applicator once water is dry. Apply generously on nose, chin, forehead and cheeks. Avoid contact with your eyes, eye-brows and lip around.
3. Allow the mask to set on your skin for 20 - 30 minutes, and then peel off the mask starting from the bottom and moving up slowly when it is become dry.

4. Rinse face with warm water to remove remaining bits of mask.
5. Recommended usage is once a week.

Storage Condition

Store below 30◦C